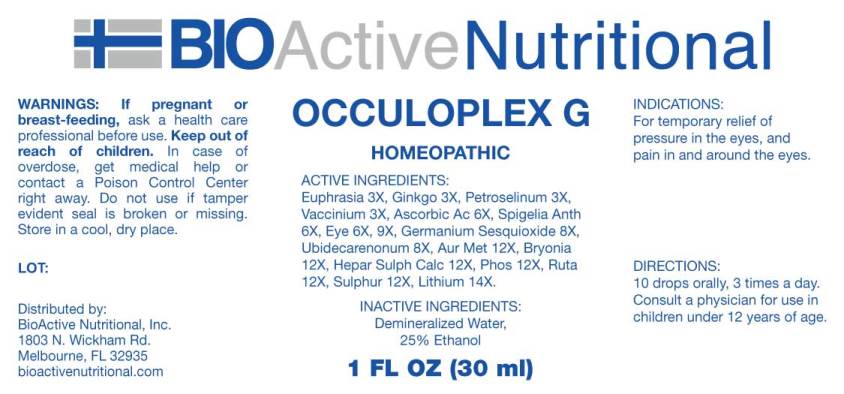 DRUG LABEL: Occuloplex G
NDC: 43857-0513 | Form: LIQUID
Manufacturer: BioActive Nutritional, Inc.
Category: homeopathic | Type: HUMAN OTC DRUG LABEL
Date: 20240502

ACTIVE INGREDIENTS: EUPHRASIA STRICTA 3 [hp_X]/1 mL; GINKGO 3 [hp_X]/1 mL; PETROSELINUM CRISPUM WHOLE 3 [hp_X]/1 mL; BILBERRY 3 [hp_X]/1 mL; ASCORBIC ACID 6 [hp_X]/1 mL; SPIGELIA ANTHELMIA WHOLE 6 [hp_X]/1 mL; SUS SCROFA EYE 6 [hp_X]/1 mL; GERMANIUM SESQUIOXIDE 8 [hp_X]/1 mL; UBIDECARENONE 8 [hp_X]/1 mL; GOLD 12 [hp_X]/1 mL; BRYONIA ALBA ROOT 12 [hp_X]/1 mL; CALCIUM SULFIDE 12 [hp_X]/1 mL; PHOSPHORUS 12 [hp_X]/1 mL; RUTA GRAVEOLENS FLOWERING TOP 12 [hp_X]/1 mL; SULFUR 12 [hp_X]/1 mL; LITHIUM 14 [hp_X]/1 mL
INACTIVE INGREDIENTS: WATER; ALCOHOL

DRUG FACTS:

ACTIVE INGREDIENTS:

Euphrasia Officinalis 3X, Ginkgo Biloba 3X, Petroselinum Sativum 3X, Vaccinium Myrtillus 3X, Ascorbic Acid 6X, Spigelia Anthelmia 6X, Eye (Suis) 6X, 9X, Germanium Sesquioxide 8X, Ubidecarenonum 8X, Aurum Metallicum 12X, Bryonia (Alba) 12X, Hepar Sulphuris Calcareum 12X, Phosphorus 12X, Ruta Graveolens 12X, Sulphur 12X, Lithium Metallicum 14X.

INDICATIONS:

For temporary relief of pressure in the eyes, and pain in and around the eyes.

WARNINGS:

If pregnant or breast-feeding, ask a health care professional before use.

Keep out of reach of children. In case of overdose, get medical help or contact a Poison Control Center right away.

Do not use if tamper evident seal is broken or missing.

Store in cool, dry place.

KEEP OUT OF REACH OF CHILDREN:

In case of overdose, get medical help or contact a Poison Control Center right away.

DIRECTIONS:

10 drops orally, 3 times a day. Consult a physician for use in children under 12 years of age.

INDICATIONS:

For temporary relief of pressure in the eyes, and pain in and around the eyes.

INACTIVE INGREDIENTS:

Demineralized Water, 25% Ethanol.

QUESTIONS:

Distributed by:

BioActive Nutritional, Inc.

1803 N. Wickham Rd.

Melbourne, FL 32935

bioactivenutritional.com

PACKAGE LABEL DISPLAY:

BIOActive Nutritional

OCCULOPLEX G

HOMEOPATHIC

1 FL OZ (30 ml)